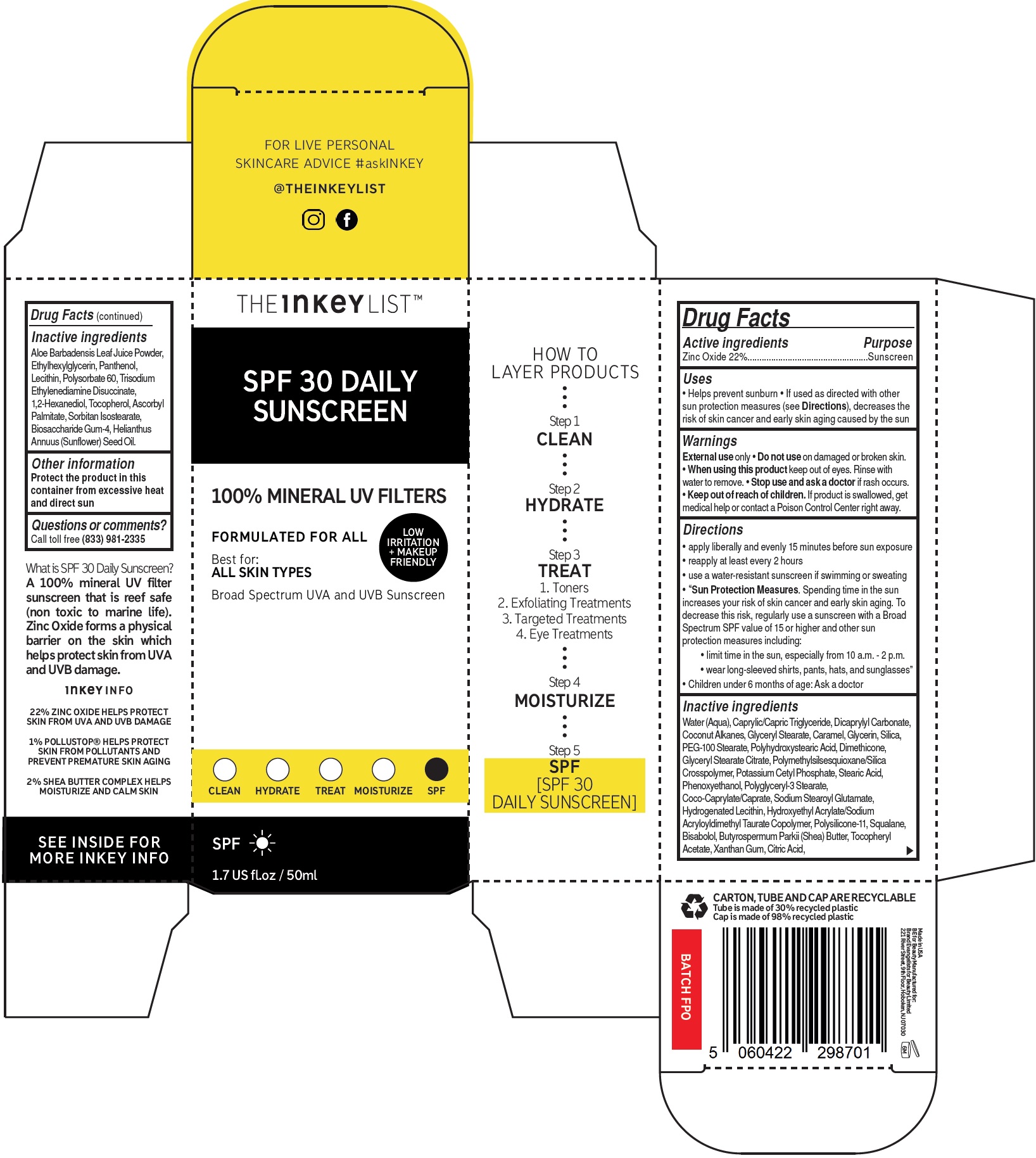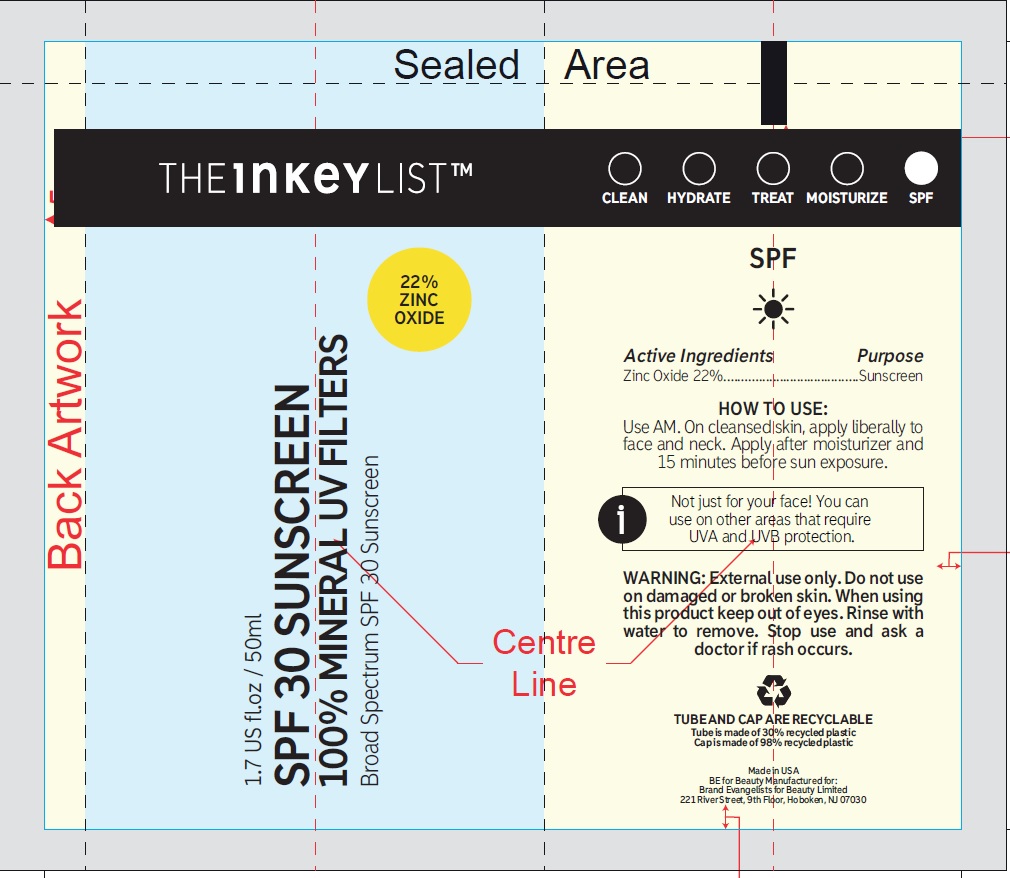 DRUG LABEL: SPF 30 Daily Sunscreen
NDC: 81136-001 | Form: CREAM
Manufacturer: Brand Evangelists for Beauty Ltd.
Category: otc | Type: HUMAN OTC DRUG LABEL
Date: 20240226

ACTIVE INGREDIENTS: ZINC OXIDE 220 mg/1 mL
INACTIVE INGREDIENTS: WATER; MEDIUM-CHAIN TRIGLYCERIDES; DICAPRYLYL CARBONATE; COCONUT ALKANES; GLYCERYL MONOSTEARATE; CARAMEL; GLYCERIN; SILICON DIOXIDE; PEG-100 STEARATE; POLYHYDROXYSTEARIC ACID (2300 MW); DIMETHICONE; GLYCERYL STEARATE CITRATE; POLYMETHYLSILSESQUIOXANE (4.5 MICRONS); POTASSIUM CETYL PHOSPHATE; STEARIC ACID; PHENOXYETHANOL; POLYGLYCERYL-3 STEARATE; COCOYL CAPRYLOCAPRATE; SODIUM STEAROYL GLUTAMATE; HYDROGENATED SOYBEAN LECITHIN; HYDROXYETHYL ACRYLATE/SODIUM ACRYLOYLDIMETHYL TAURATE COPOLYMER (100000 MPA.S AT 1.5%); DIMETHICONE/VINYL DIMETHICONE CROSSPOLYMER (SOFT PARTICLE); SQUALANE; LEVOMENOL; SHEA BUTTER; .ALPHA.-TOCOPHEROL ACETATE; XANTHAN GUM; CITRIC ACID MONOHYDRATE; ALOE VERA LEAF; ETHYLHEXYLGLYCERIN; PANTHENOL; POLYSORBATE 60; TRISODIUM ETHYLENEDIAMINE DISUCCINATE; 1,2-HEXANEDIOL; TOCOPHEROL; ASCORBYL PALMITATE; SORBITAN ISOSTEARATE; BIOSACCHARIDE GUM-4; SUNFLOWER OIL

SPF 30 Daily Sunscreen

Active ingredients

Zinc Oxide 22%

Purpose

Sunscreen

Uses

- Helps prevent sunburn
- If used as directed with other sun protection measures (see), decreases the risk of skin cancer and early skin aging caused by the sun Directions

Warnings

only External use

Do not use

- on damaged or broken skin.

When using this product

- keep out of eyes. Rinse with water to remove.

Stop use and ask a doctor

- if rash occurs

Keep out of reach of children.

- If product is swallowed, get medical help or contact a Poison Control Center right away.

Directions

- apply liberally and evenly 15 minutes before sun exposure
- reapply at least every 2 hours
- use a water-resistant sunscreen if swimming or sweating
- Spending time in the sun increases your risk of skin cancer and early skin aging. To decrease this risk, regularly use a sunscreen with a Broad Spectrum SPF value of 15 or higher and other sun protection measures including: • limit time in the sun, especially from 10 a.m. - 2 p.m. • wear long-sleeved shirts, pants, hats, and sunglasses” “Sun Protection Measures.
- Children under 6 months of age: Ask a doctor

Inactive ingredients

Water (Aqua), Caprylic/Capric Triglyceride, Dicaprylyl Carbonate, Coconut Alkanes, Glyceryl Stearate, Caramel, Glycerin, Silica, PEG-100 Stearate, Polyhydroxystearic Acid, Dimethicone, Glyceryl Stearate Citrate, Polymethylsilsesquioxane/Silica Crosspolymer, Potassium Cetyl Phosphate, Stearic Acid, Phenoxyethanol, Polyglyceryl-3 Stearate, Coco-Caprylate/Caprate, Sodium Stearoyl Glutamate, Hydrogenated Lecithin, Hydroxyethyl Acrylate/Sodium Acryloyldimethyl Taurate Copolymer, Polysilicone-11, Squalane, Bisabolol, Butyrospermum Parkii (Shea) Butter, Tocopheryl Acetate, Xanthan Gum, Citric Acid,Aloe Barbadensis Leaf Juice Powder, Ethylhexylglycerin, Panthenol, Lecithin, Polysorbate 60, Trisodium Ethylenediamine Disuccinate, 1,2-Hexanediol, Tocopherol, Ascorbyl Palmitate, Sorbitan Isostearate, Biosaccharide Gum-4, Helianthus Annuus (Sunflower) Seed Oil.

Other information

Protect the product in this container from excessive heat and direct sun

Questions or comments?

Call toll free (833) 981-2335